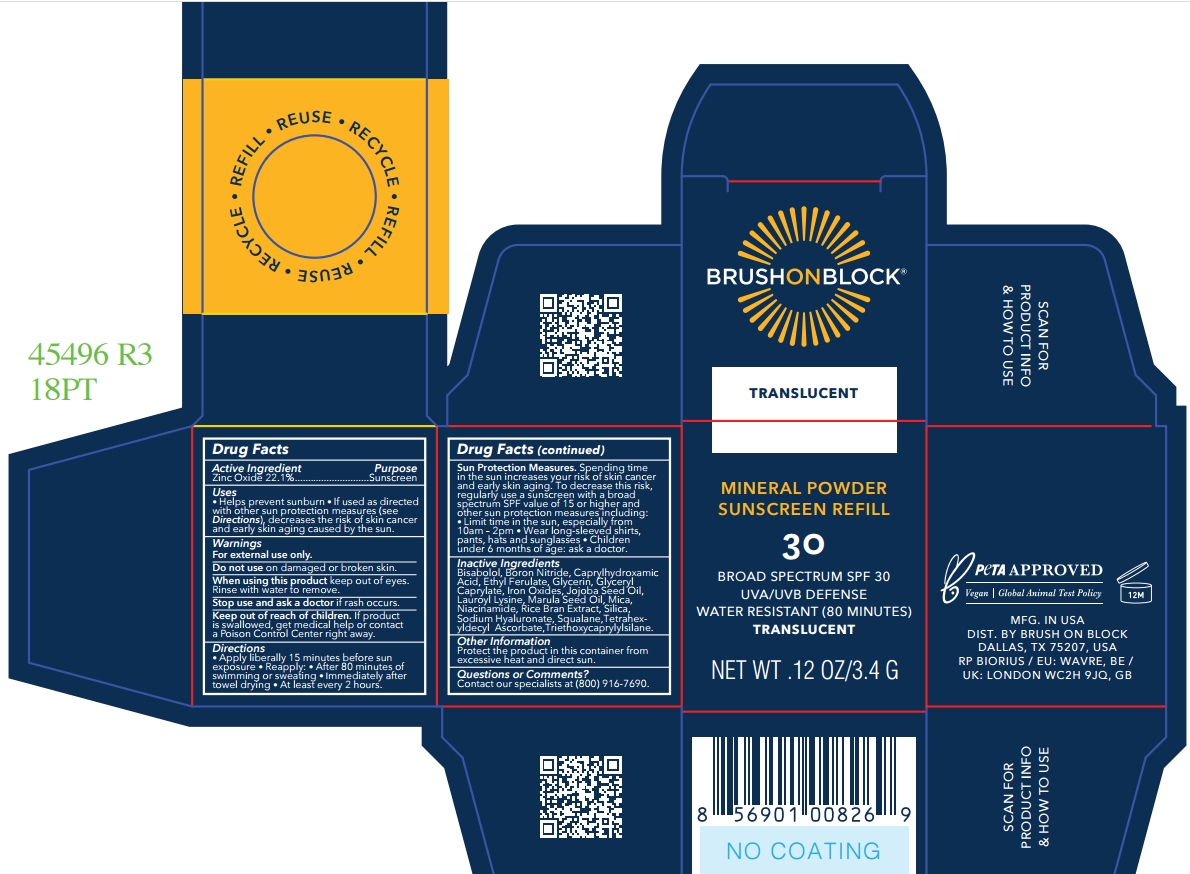 DRUG LABEL: Brush On Block SPF 30 Mineral Powder Translucent Zinc Only-Refill
NDC: 58274-023 | Form: POWDER
Manufacturer: SPF Ventures, LLC
Category: otc | Type: HUMAN OTC DRUG LABEL
Date: 20250203

ACTIVE INGREDIENTS: ZINC OXIDE 22.1 g/100 g
INACTIVE INGREDIENTS: BORON NITRIDE; ORYZA SATIVA (RICE) BRAN; CI 77492; SCLEROCARYA BIRREA SEED OIL; GLYCERIN; MICA; SILICA; SODIUM HYALURONATE; NIACINAMIDE; GLYCERYL CAPRYLATE; CI 77491; LAUROYL LYSINE; CI 77499; SIMMONDSIA CHINENSIS (JOJOBA) SEED OIL; SQUALANE; TRIETHOXYCAPRYLYLSILANE; TETRAHEXYLDECYL ASCORBATE; CAPRYLHYDROXAMIC ACID; ETHYL FERULATE; BISABOLOL

Brush On Block SPF 30 Mineral Powder Translucent Zinc Only-Refill

Active ingredient

Zinc Oxide 22.1%

Purpose

Sunscreen

Uses

- Helps prevent sunburn
- If used as directed with other sun protection measures (see Directions), decreases the risk of skin cance and early skin aging caused by the sun.

Warnings

For external use only.

Do not use on damaged or broken skin.

When using this product keep out of eyes. Rinse with water to remove.

Stop use and ask a doctor if rash occurs.

Keep out of reach of children

If product is swallowed, get medical help or contact a Poison Control Center right away.

Directions

- Apply liberally 15 minutes before sun exposure
- Reapply: After 80 minutes of swimming or sweating; Immediately after towel drying; At least every 2 hours.

Sun Protection Measures. Spending time in the sun increases your risk of skin cance and early skin aging. To decrease this risk, regularly use a sunscreen with a broad spectrum SPF value of 15 or higher and other sun protection measures including:Limit time in the sun especially from 10am-2pm; Wear long-sleeved shirts, pants, hats and subglasses; Children under 6 months: ask a doctor.

Inactive Ingredients

Sodium hyaluronate

Niacinimide

Mica

Lauroyl lysine

Boron nitride

Silica

Triethoxycaprylylsilane

Ethyl ferulate

Oryza sativa (rice) bran extract

Iron oxides (CI 77492)

Iron oxides (CI 77499)

Iron oxides (CI 77491)

Bisabolol

Squalane

Simmondsia chinensis (jojoba) seed oil

Tetrahexyldecyl ascorbate

Sclerocarya birrea seed oil

Glyceryl caprylate

Glycerin

Caprylhydroxamic acid

Other information

Protect the product in this container from excessive heat and direct sun.